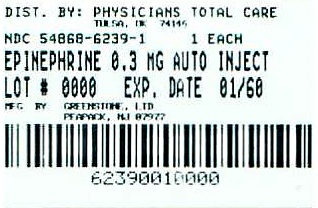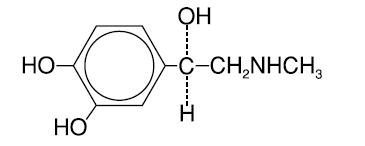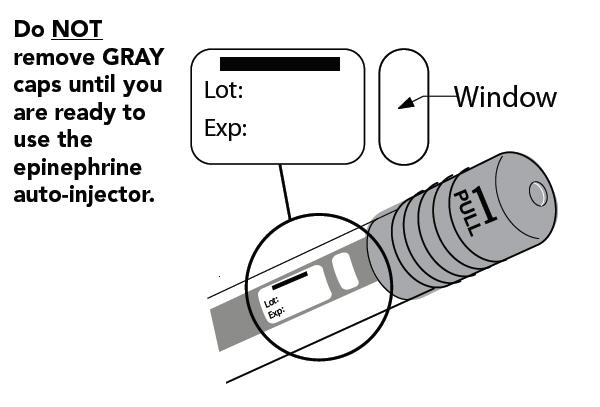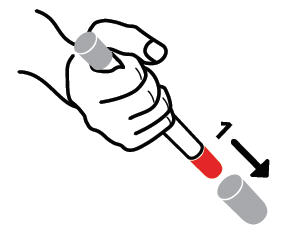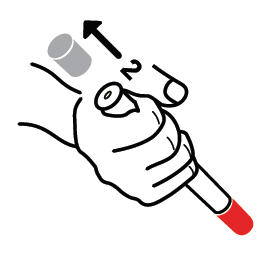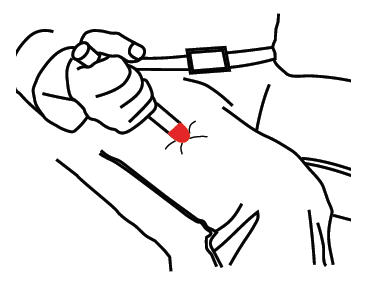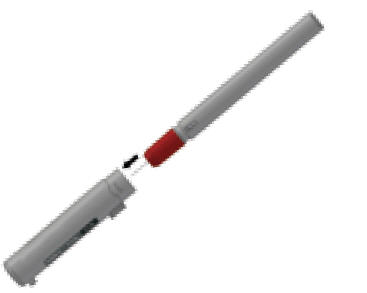 DRUG LABEL: EPINEPHRINE
NDC: 54868-6239 | Form: INJECTION
Manufacturer: Physicians Total Care, Inc.
Category: prescription | Type: HUMAN PRESCRIPTION DRUG LABEL
Date: 20110216

ACTIVE INGREDIENTS: EPINEPHRINE 0.3 mg/1 1
INACTIVE INGREDIENTS: SODIUM CHLORIDE; CHLOROBUTANOL; SODIUM BISULFITE

epinephrine injection, USP
auto-injector

PRESCRIBING INFORMATION

Available as 0.15 mg 0.3 mg

each unit delivers 0.15 mg or 0.3 mg of epinephrine

DESCRIPTION

Epinephrine injection, USP auto-injector (referred to throughout as epinephrine auto-injector) contains 1.1 mL epinephrine injection, USP (1 mg/mL), from which one dose of either 0.15 mg (0.15 mL) or 0.3 mg (0.3 mL) each is available for use by injection. The dose is administered by auto-injection after the patient prepares and fires epinephrine auto-injector as directed. The remaining volume is not available for use and should be discarded. See PATIENT DIRECTIONS FOR USE on the accompanying Patient Information Leaflet.

This single, available dose of epinephrine injection, USP contains either 0.15 mg or 0.3 mg l-epinephrine, sodium chloride, chlorobutanol and sodium bisulfite, all sealed under nitrogen.

Epinephrine is a sympathomimetic catecholamine. Its naturally occurring l-isomer, which is twenty times as active as the d-isomer, is obtained in pure form by separation from the synthetically produced racemate.

Chemically, epinephrine is 1-(3,4-dihydroxyphenyl)-2-(methylamino)ethanol with the following structure:

Epinephrine deteriorates rapidly on exposure to air or light, turning pink from oxidation to adrenochrome and brown from the formation of melanin. Epinephrine solutions that show evidence of discoloration should be discarded.

Epinephrine auto-injector contains no latex.

CLINICAL PHARMACOLOGY

Epinephrine is the drug of choice for the emergency treatment of severe allergic reactions (Type I) to allergens, such as those present in certain insect venoms, foods, or drugs. It can also be used in the treatment of anaphylaxis of unknown cause (idiopathic anaphylaxis) or exercise-induced anaphylaxis. Epinephrine, when given intramuscularly or subcutaneously, has a rapid onset and short duration of action. Epinephrine acts on both alpha and beta adrenergic receptors. Through its action on alpha adrenergic receptors, epinephrine lessens the vasodilation and increased vascular permeability that occurs during an anaphylactic reaction and can lead to loss of intravascular fluid volume and hypotension. Through its action on beta adrenergic receptors, epinephrine causes bronchial smooth muscle relaxation that helps alleviate bronchospasm, wheezing, and dyspnea that may occur during anaphylaxis. Epinephrine also helps alleviate pruritus, urticaria, and angioedema, and may be effective in relieving gastrointestinal and genitourinary symptoms of anaphylaxis because of its relaxer effects on the smooth muscle of the stomach, intestine, uterus and urinary bladder.

INDICATIONS AND USAGE

Epinephrine auto-injector is indicated in the emergency treatment of severe allergic reactions (Type I) including anaphylaxis to stinging insects (e.g. order Hymenoptera, which includes bees, wasps, hornets, yellow jackets and fire ants), and biting insects (e.g. triatoma, mosquitos), allergen immunotherapy, foods, drugs, diagnostic testing substances (e.g. radiocontrast media), and other allergens, as well as anaphylaxis to unknown substances (idiopathic anaphylaxis) or exercise-induced anaphylaxis. Epinephrine auto-injector is intended for immediate administration in patients with a history of anaphylactic reactions. Selection of the appropriate dosage strength is determined according to patient body weight (See DOSAGE AND ADMINISTRATION section).

Such reactions may occur within minutes after exposure and consist of flushing, apprehension, syncope, tachycardia, thready or unobtainable pulse associated with a fall in blood pressure, convulsions, vomiting, diarrhea and abdominal cramps, involuntary voiding, wheezing, dyspnea due to laryngeal spasm, pruritus, rashes, urticaria, or angioedema. Epinephrine auto-injector is designed as emergency supportive therapy only and is not a replacement or substitute for immediate medical care.

CONTRAINDICATIONS

There are no absolute contraindications to the use of epinephrine in a life-threatening allergic reaction.

WARNINGS

Epinephrine auto-injector should only be injected into the anterolateral aspect of the thigh. Accidental injection into the hands or feet may result in loss of blood flow to the affected area and should be avoided. DO NOT INJECT INTO BUTTOCK. If there is an accidental injection into these areas, advise the patient to inform the healthcare provider of the accidental injection when he/she goes to the nearest emergency room for further treatment of anaphylaxis.

Avoid possible inadvertent intravascular administration. Large doses or accidental intravenous injection of epinephrine may result in cerebral hemorrhage due to a sharp rise in blood pressure. DO NOT INJECT INTRAVENOUSLY. Rapidly acting vasodilators can counteract the marked pressor effects of epinephrine if there is such inadvertent administration.

Epinephrine is the preferred treatment for serious allergic reactions or other emergency situations even though this product contains sodium bisulfite, a sulfite that may, in other products, cause allergic-type reactions including anaphylactic symptoms or life-threatening or less severe asthmatic episodes in certain susceptible persons. The alternatives to using epinephrine in a life-threatening situation may not be satisfactory. The presence of a sulfite in this product should not deter administration of the drug for treatment of serious allergic or other emergency situations, even if the patient is sulfite-sensitive.

Epinephrine should be administered with caution to patients with cardiac arrhythmias, coronary artery or organic heart disease, or hypertension. In patients with coronary insufficiency or ischemic heart disease, epinephrine may precipitate or aggravate angina pectoris as well as produce ventricular arrhythmias. It should be recognized that the presence of these conditions is not a contraindication to epinephrine administration in an acute, life-threatening situation.

Epinephrine is light sensitive and should be stored in the carrying-case provided. Store at room temperature (20°-25°C/68°-77°F) with excursions permitted to 15°-30°C (59°-86°F). Do not refrigerate; protect from freezing. Patients should periodically check the solution in epinephrine auto-injector for any discoloration and/or precipitates. If the solution is discolored or contains a precipitate, the patient should replace their epinephrine auto-injector.

PRECAUTIONS

(1) General

Epinephrine auto-injector is not intended as a substitute for immediate medical care. In conjunction with the administration of epinephrine, the patient should seek appropriate medical care. More than two sequential doses of epinephrine should only be administered under direct medical supervision.

Epinephrine is essential for the treatment of anaphylaxis. Patients with a history of severe allergic reactions should be instructed about the circumstances under which epinephrine should be used (See INDICATIONS AND USAGE Section). It should be determined that the patient is at risk of future anaphylaxis, since there are some concerns in specific patients with epinephrine administration. (a) Epinephrine should be used with caution in patients with cardiac arrhythmias, coronary artery or organic heart disease, hypertension, or in patients who are on medications that may sensitize the heart to arrhythmias, e.g., digitalis, diuretics, or anti-arrhythmics. In such patients, epinephrine may precipitate or aggravate angina pectoris as well as produce ventricular arrhythmias. (b) The effects of epinephrine may be potentiated by tricyclic antidepressants and monoamine oxidase inhibitors. (c) Some patients may be at greater risk of developing adverse reactions after epinephrine administration. These include patients with hyperthyroidism, cardiovascular disease, hypertension, diabetes, and elderly individuals, and pregnant women. It must be noted that, despite these concerns, epinephrine is essential for the treatment of anaphylaxis. Therefore, patients with these conditions, or any other person who might be in a position to administer epinephrine to a patient with these conditions experiencing anaphylaxis, should be instructed about the circumstances under which epinephrine should be used.

(2) Information for Patients

Complete patient information, including dosage, directions for proper administration, and precautions, can be found inside each epinephrine auto-injector package within the Patient Information Leaflet.

Epinephrine may produce symptoms and signs that include an increase in pulse rate, the sensation of a more forceful heartbeat, palpitations, a throbbing headache, pallor, feelings of overstimulation, anxiety, weakness, shakiness, dizziness, or nausea. These signs and symptoms usually subside rapidly, especially with rest, quiet, and recumbency. Patients with hypertension or hyperthyroidism may develop more severe or persistent effects, and patients with coronary artery disease could experience angina. Patients with diabetes may develop increased blood glucose levels following epinephrine administration. Patients with Parkinson's disease may notice a temporary worsening of symptoms.

(3) Drug Interactions

Patients who receive epinephrine while concomitantly taking cardiac glycosides or diuretics should be observed carefully for the development of cardiac arrhythmias.

The effects of epinephrine may be potentiated by tricyclic antidepressants, monoamine oxidase inhibitors, sodium levothyroxine, and certain antihistamines, notably chlorpheniramine, tripelennamine, and diphenhydramine.

The cardiostimulating and bronchodilating effects of epinephrine are antagonized by beta-adrenergic blocking drugs, such as propranolol. The vasoconstricting and hypertensive efffects are antagonized by alpha-adrenergic blocking drugs, such as phentolamine. Ergot alkaloids and phenothiazines may also reverse the pressor effects of epinephrine.

(4) Carcinogenesis, Mutagenesis, Impairment of Fertility

There are no data from either animal or human studies regarding the carcinogenicity or mutagenicity of epinephrine, and no studies have been conducted to determine its potential for the impairment of fertility. This should not prevent the use of epinephrine under the conditions noted under INDICATIONS AND USAGE section.

(5) Pregnancy

Pregnancy Category C

Epinephrine has been shown to have developmental effects in rabbits at a subcutaneous dose of 1.2 mg/kg (approximately 30 times the maximum recommended daily subcutaneous or intramuscular dose on a mg/m2 basis), in mice at a subcutaneous dose of 1 mg/kg (approximately 7 times the maximum recommended daily subcutaneous or intramuscular dose on a mg/m2 basis), and in hamsters at a subcutaneous dose of 0.5 mg/kg (approximately 5 times the maximum recommended daily subcutaneous or intramuscular dose on a mg/m2 basis). These effects were not seen in mice at a subcutaneous dose of 0.5 mg/kg (approximately 3 times the maximum recommended daily subcutaneous or intramuscular dose on a mg/m2 basis). Although there are no adequate and well-controlled studies in pregnant women, epinephrine crosses the placenta and could lead to fetal anoxia, spontaneous abortion or both. Therefore, epinephrine should be used in pregnancy only if the potential benefit justifies the potential risk to the fetus.

ADVERSE REACTIONS

Adverse reactions to epinephrine include transient, moderate anxiety; apprehensiveness; restlessness; tremor; weakness; dizziness; sweating; palpitations; pallor; nausea and vomiting; headache, and/or respiratory difficulties. These symptoms occur in some persons receiving therapeutic doses of epinephrine, but are more likely to occur in patients with hypertension or hyperthyroidism. Large doses of epinephrine can cause acute hypertension. Arrhythmias, including fatal ventricular fibrillation, have been reported, particularly in patients with underlying cardiac disease or those receiving certain drugs [see (3) Drug Interactions]. Rapid rises in blood pressure have produced cerebral hemorrhage, particularly in elderly patients with cardiovascular disease. Angina may occur in patients with coronary artery disease. The potential for epinephrine to produce these types of adverse reactions does not contraindicate its use in an acute, life-threatening allergic reaction.

OVERDOSAGE

Epinephrine is rapidly inactivated in the body, and treatment following overdose with epinephrine is primarily supportive. If necessary, pressor effects may be counteracted by rapidly acting vasodilators or alpha-adrenergic blocking drugs. If prolonged hypotension follows such measures, it may be necessary to administer another pressor drug.

Overdosage of epinephrine may produce extremely elevated arterial pressure, which may result in cerebrovascular hemorrhage, particularly in elderly patients.

If an epinephrine overdose induces pulmonary edema that interferes with respiration, treatment consists of a rapidly acting alpha-adrenergic blocking drug and/or respiratory support.

Epinephrine overdosage can also cause transient bradycardia followed by tachycardia, and these may be accompanied by potentially fatal cardiac arrhythmias. Premature ventricular contractions may appear within one minute after injection and may be followed by multifocal ventricular tachycardia (prefibrillation rhythm). Subsidence of the ventricular effects may be followed by atrial tachycardia and occasionally by atrioventricular block. Treatment of arrhythmias consists of administration of a beta-adrenergic blocking drug such as propranolol.

Overdosage sometimes results in extreme pallor and coldness of the skin, metabolic acidosis, and kidney failure. Suitable corrective measures must be taken in such situations.

DOSAGE AND ADMINISTRATION

The physician who prescribes epinephrine auto-injector should review this Prescribing Information insert in detail with the patient. This review should include the proper use of epinephrine auto-injector to ensure that subcutaneous or intramuscular injections are given into the anterolateral aspect of the thigh, through clothing if necessary. The accompanying Patient Information Leaflet and Wrap Label should also be reviewed with the patient.

Epinephrine auto-injector is capable of delivering one dose of either 0.15 mg or 0.3 mg (0.15 mL or 0.3 mL of epinephrine). This dose is available for auto-injection by the patient.

Selection of the appropriate epinephrine auto-injector dosage strength is determined according to patient body weight.

Epinephrine auto-injector 0.15 mg | For use by patients who weigh 15 - 30 kilograms (approximately 33 - 66 pounds)
Epinephrine auto-injector 0.3 mg | For use by patients who weigh 30 kilograms (approximately 66 pounds) or greater

The usual dose of epinephrine for allergic emergencies in patients who weigh 30 kilograms or greater is 0.3 mg (0.3 mL of epinephrine).

Since the doses of epinephrine delivered from epinephrine auto-injector are fixed, the physician should consider other forms of injectable epinephrine if doses lower than those available from epinephrine auto-injector are felt to be necessary. The prescribing physician should carefully assess each patient to determine the most appropriate dose of epinephrine, recognizing the life-threatening nature of the reactions for which this drug is being prescribed.

Patients should be instructed to periodically visually inspect the epinephrine solution for particulate matter and discoloration. If the solution contains particulate matter or develops a pinkish color or becomes darker than slightly yellow, the patient should immediately contact their physician for a replacement, since these changes indicate that the effectiveness of the drug product may be decreased.

HOW SUPPLIED

Epinephrine auto-injector is a patient (or caregiver) actuated product that contains 1.1 mL of epinephrine injection, USP (1 mg/mL), of which one dose can be delivered by auto-injection. THE REMAINING VOLUME THAT IS LEFT AFTER THIS FIXED DOSE CANNOT BE FURTHER ADMINISTERED AND SHOULD BE DISCARDED WITH THE DEVICE AS OUTLINED IN THE PATIENT INFORMATION LEAFLET.

Epinephrine auto-injector 0.3 mg is available in a

Single unit carton, NDC 54868-6239-1, containing one epinephrine auto-injector 0.3 mg;

Two-Pack carton, NDC 54868-6239-0, containing two epinephrine auto-injectors 0.3 mg.

STORAGE AND HANDLING

PROTECT FROM LIGHT. STORE AT ROOM TEMPERATURE, 20°-25°C (68°-77°F) WITH EXCURSIONS PERMITTED TO 15°-30°C (59°-86°F). PROTECT FROM FREEZING. DO NOT REFRIGERATE.

Rx only.

GREENSTONE® BRAND

Distributed by:
Greenstone LLC
Peapack, NJ 07977

Printed in USA

For inquiries call 1-800-438-1985

Revised January, 2010

Relabeling of "Additional" barcode label by:
Physicians Total Care, Inc.
Tulsa, OK 74146

Patient Information

epinephrine injection, USP auto-injector

Authorized generic of Adrenaclick

The patient, and caregiver, if possible, should read this information carefully before using epinephrine injection, USP auto-injector (referred to throughout as epinephrine auto-injector). You must know how to use epinephrine auto-injector before you have an emergency. This information contains additional details beyond the quick-reference instructions on the epinephrine auto-injector label. This information does not replace talking with your doctor about your medical condition or your treatment.

What is the most important information I should know about epinephrine auto-injector?

Use epinephrine auto-injector and go to your doctor or emergency room right away for more medical treatment.

- Epinephrine, the active ingredient in epinephrine auto-injector helps treat life-threatening allergic reactions.
- Make sure to tell your doctor about all your medical conditions and allergies.
- Always get medical treatment right away after using epinephrine auto-injector.

Since you cannot predict when a life-threatening allergic reaction will occur, carry epinephrine auto-injector with you at all times.

Look at the medicine in your epinephrine auto-injector regularly. If it looks cloudy (has particles in it), is discolored, or if the expiration date has passed, the epinephrine auto-injector should be replaced.

After administration, liquid will remain in the auto-injector that can't be used and should be discarded with the auto-injector as outlined in this Patient Information Leaflet.

What is epinephrine auto-injector?

Epinephrine auto-injector is an emergency injection ("shot") of epinephrine. It is a medicine used for life-threatening allergic reactions such as severe swelling, breathing problems, or loss of blood pressure. Allergic reactions can be caused by stinging and biting insects (bugs), allergy injections, food, medicines, exercise, or unknown causes.

Life-threatening allergic reactions may show up as closing of your breathing airways, wheezing, sneezing, hoarseness, hives, itching, swelling, skin redness, fast heartbeat, weak pulse, feeling very anxious, confusion, stomach pain, losing control of urine or bowel movements (incontinence), faintness, or "passing out" (unconsciousness).

- Epinephrine auto-injector 0.15mg is for patients who weigh 33-66 pounds (15-30 kg).
- Epinephrine auto-injector 0.3mg is for patients who weigh 66 pounds (30 kg) or greater.
- Use of epinephrine auto-injector must be followed by emergency medical care.
- Each epinephrine auto-injector unit contains a single dose of epinephrine.

Who should not use epinephrine auto-injector?

There are no absolute contraindications to the use of epinephrine auto-injector in a life-threatening allergic reaction. People with certain medical conditions have a higher chance of getting serious side effects from epinephrine auto-injector.

Tell your doctor about all your medical conditions, but especially if you:

- have heart disease or high blood pressure
- have diabetes
- have thyroid conditions
- have asthma
- have depression or other mental disease
- have Parkinson's disease
- are pregnant
- are allergic to any of the ingredients in epinephrine auto-injector

Tell your doctor about all the medicines you take, including prescription and non-prescription medicines, vitamins and herbal supplements. Some medicines may cause serious side effects if taken while you use epinephrine auto-injector. Some medicines may affect how epinephrine auto-injector works, or epinephrine auto-injector may affect how your other medicines work. Diabetic patients may need to adjust the dose of their diabetes medicines or insulin after using epinephrine auto-injector.

How should I use epinephrine auto-injector?

- Do NOT remove the gray caps until you are ready to use.
- Never put thumb, fingers, or hand over the red tip. The needle comes out of the red tip. Accidental injection into hand or feet may result in the loss of blood flow to these areas. If this happens, go immediately to the nearest emergency room.
- Hold epinephrine auto-injector in the thigh while slowly counting to 10 to make sure all medicine is delivered.
- Inject epinephrine auto-injector only into the middle of the outer side of your thigh (upper leg).

What should I avoid while using epinephrine auto-injector?

- Avoid injecting epinephrine auto-injector into your buttock or any other part of your body, other than the middle of the outer side of your thigh (upper leg).
- Avoid injecting epinephrine auto-injector into a vein.

What are the possible side effects of epinephrine auto-injector?

Too much epinephrine (epinephrine auto-injector) can cause dangerously high blood pressure, stroke, or death.

If you take certain medicines, you may develop serious life-threatening side effects from the epinephrine in epinephrine auto-injector. Be sure to tell your doctor about all the medicines you take, especially medicines for asthma.

Patients with certain medical conditions, or who take certain medicines, may get more side effects from epinephrine auto-injector, or the side effects may last longer. This includes patients who take certain types of medicines for asthma, allergies, depression, hyperthyroidism, high blood pressure, and heart disease. Patients with heart disease may feel chest pain (angina). Patients with mental disease or Parkinson's disease may have worsening symptoms of their illness. Epinephrine auto-injector (epinephrine) can cause the following reactions. Some reactions can be serious. They usually go away with rest.

Common side effects of epinephrine auto-injector include:

- faster, irregular (wrong) or 'pounding' heartbeat
- throbbing headache
- paleness
- feelings of over excitement, anxiety, or fear
- weakness or shakiness
- dizziness
- nausea and vomiting
- sweating

These are not all the possible side effects of epinephrine auto-injector. For more information, ask your doctor or pharmacist.

How should I store epinephrine auto-injector?

The medicine in epinephrine auto-injector can be damaged by light. Therefore, keep it in the protective carrying case provided. Keep it at room temperature and protect it from freezing. Do not refrigerate.

Keep epinephrine auto-injector with you at all times.

Check your epinephrine auto-injector regularly to be sure:

- it has not expired
- the medicine in epinephrine auto-injector is not cloudy, discolored, or has particles in it.

Replace the epinephrine auto-injector if needed.

General information about the safe and effective use of epinephrine auto-injector.

Medicines are sometimes prescribed for conditions that are not mentioned in patient information leaflets. Do not use epinephrine auto-injector for a condition for which it was not prescribed. Do not give epinephrine auto-injector to other people, even if they have the same symptons you have. It may harm them.

This leaflet summarizes the most important information about epinephrine auto-injector. If you would like more information, talk with your doctor. You can ask your pharmacist or doctor for information about epinephrine auto-injector that is written for health professionals.

Rx only

GREENSTONE® BRAND

Distributed by:
Greenstone LLC
Peapack, NJ 07977

Printed in U.S.A.

71007-01

Patient Directions for Use

Before Use Make Sure Medicine Is Ready When You Need It

Look at the medicine in the epinephrine auto=injector regularly. If it looks cloudy, is discolored, has particles in it, or if the expiration date has passed, the epinephrine auto-injector should be replaced.

The following instructions should be followed for both epinephrine auto-injector 0.15mg and epinephrine auto-injector 0.3mg.

STEP A

- Pull off GRAY end cap with the [1]; you will now see a RED tip. Never put thumb, finger, or hand over the RED tip.
- Pull off GRAY end cap with [2].

STEP B

- Put the RED tip against the middle of the outer side of your thigh (upper leg) as shown. It can go through clothes.
- Press down hard until the needle enters your thigh (upper leg) through your skin. Hold it in place while slowly counting to 10.
- Remove the epinephrine auto-injector from your thigh.
- Check the RED tip. If the needle is exposed you received the dose. If needle is not visible, repeat Step B.

Get emergency medical help right away.

Call 911

AFTER USE/DISPOSAL

- The remaining liquid that is left after this fixed dose cannot be further administered and should be discarded.
- Put the auto-injector, needle first, into the carrying case.
- Put the light gray case top over the non-needle end of the epinephrine auto-injector unit and close the case.
- Give your used epinephrine auto-injector to a healthcare worker for proper disposal. Do NOT throw away in a regular trash can.

PRINCIPAL DISPLAY PANEL

NDC 54868-6239-1

Contains One 0.3 mg Auto-Injector

GREENSTONE® BRAND

epinephrine injection, USP

auto-injector

0.3 mg

For Subcutaneous or Intramuscular Use Only

For Allergic Emergencies
(Anaphylaxis)

Rx only